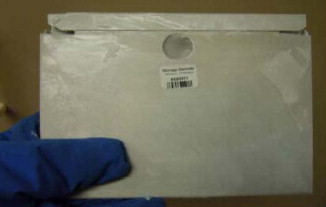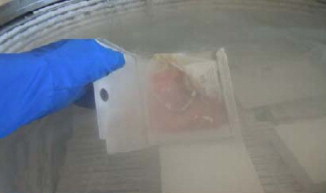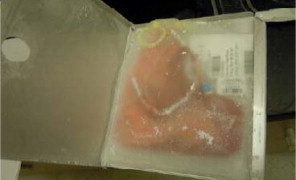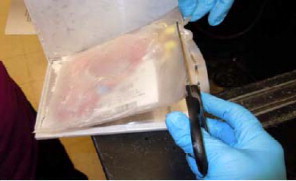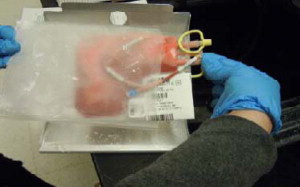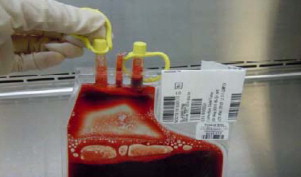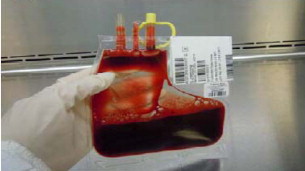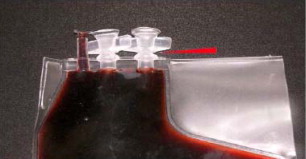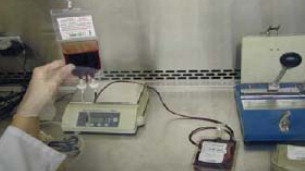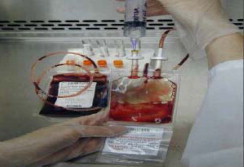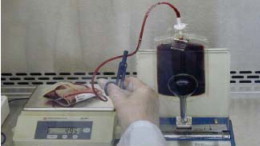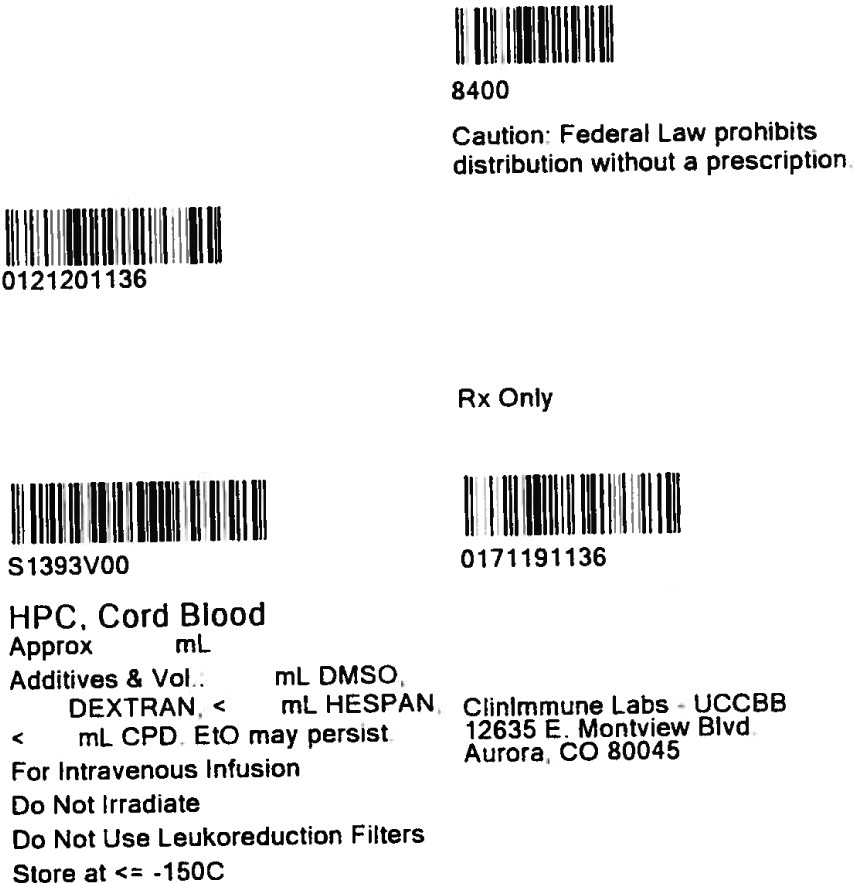 DRUG LABEL: Hematopoietic Progenitor Cells, Cord Blood
NDC: W3213-S1393 | Form: LIQUID
Manufacturer: Clinimmune Labs, University of Colorado Blood Bank
Category: other | Type: LICENSED MINIMALLY MANIPULATED CELLS LABEL
Date: 20250410

ACTIVE INGREDIENTS: HUMAN CORD BLOOD HEMATOPOIETIC PROGENITOR CELL 500000000 1/30 mL
INACTIVE INGREDIENTS: Hetastarch; sodium chloride; Dextran 40; Dimethyl Sulfoxide

HIGHLIGHTS OF PRESCRIBING INFORMATION

These highlights do not include all the information needed to use HPC, Cord Blood safely and effectively. See full prescribing information for HPC, Cord Blood.
HPC, Cord Blood
Injectable Suspension for Intravenous Use
Initial U.S. Approval: 2012

WARNING: FATAL INFUSION REACTIONS, GRAFT VERSUS HOST DISEASE, ENGRAFTMENT SYNDROME AND GRAFT FAILURE

See full prescribing information for complete boxed warning.

- Fatal infusion reactions: Monitor patients during infusion and discontinue for severe reactions. Use is contraindicated in patients with known allergy to dimethyl sulfoxide (DMSO), Dextran 40 or human serum albumin. (4, 5.1, 5.2)
- Graft-vs-host disease (GVHD): GVHD may be fatal. Administration of immunosuppressive therapy may decrease the risk of GVHD. (5.3)
- Engraftment syndrome: Engraftment syndrome may be fatal. Treat engraftment syndrome promptly with corticosteroids. (5.4)
- Graft failure: Graft failure may be fatal. Monitor patients for laboratory evidence of hematopoietic recovery. (5.5)

1 INDICATIONS AND USAGE

HPC (hematopoietic progenitor cells), Cord Blood is an allogeneic cord blood hematopoietic progenitor cell therapy indicated for use in unrelated donor hematopoietic progenitor cell transplantation procedures in conjunction with an appropriate preparative regimen for hematopoietic and immunologic reconstitution in patients with disorders affecting the hematopoietic system that are inherited, acquired, or result from myeloablative treatment. (1)

The risk benefit assessment for an individual patient depends on the patient characteristics, including disease, stage, risk factors, and specific manifestations of the disease, on characteristics of the graft, and on other available treatments or types of hematopoietic progenitor cells. (1)

2 DOSAGE AND ADMINISTRATION

- Unit selection and administration of HPC, Cord Blood should be done under the direction of a physician experienced in hematopoietic progenitor cell transplantation.
- The recommended minimum dose is 2.5 x 10^7 nucleated cells/kg at cryopreservation. (2.1)
- Do not administer HPC, Cord Blood through the same tubing with other products except for normal saline. (2.3)

3 DOSAGE FORMS AND STRENGTHS

Each unit contains a minimum of 5 x 10^8 total nucleated cells with at least 1.25 x 10^6 viable CD34+ cells at the time of cryopreservation. The exact pre-cryopreservation nucleated cell content of each unit is provided on the container label and accompanying records. (3)

4 CONTRAINDICATIONS

Known sensitivity to dimethyl sulfoxide (DMSO), Dextran 40 or plasma proteins. (4)

5 WARNINGS AND PRECAUTIONS

- Allergic Reactions and Anaphylaxis (5.1)
- Infusion Reactions (5.2)
- Graft-versus-Host Disease (5.3)
- Engraftment Syndrome (5.4)
- Graft Failure (5.5)
- Malignancies of Donor Origin (5.6)
- Transmission of Serious Infections (5.7)
- Transmission of Rare Genetic Diseases (5.8)

6 ADVERSE REACTIONS

Mortality, from all causes, at 100 days post-transplant was 25%. (6.1)

The most common infusion-related adverse reactions (≥5%) are hypertension, vomiting, nausea, bradycardia, and fever. (6.1)

To report SUSPECTED ADVERSE REACTIONS, contact ClinImmune Labs, University of Colorado Cord Blood Bank (UCCBB) at 303-724-1306 and FDA at 1-800-FDA-1088 or www.fda.gov/medwatch.

8 USE IN SPECIFIC POPULATIONS

- Pregnancy: Based on animal data, may cause fetal harm. Use only if clearly needed. (8.1)

FULL PRESCRIBING INFORMATION

WARNING: FATAL INFUSION REACTIONS, GRAFT VERSUS HOST DISEASE, ENGRAFTMENT SYNDROME AND GRAFT FAILURE

Fatal infusion reactions: HPC, Cord Blood administration can result in serious, including fatal, infusion reactions. Monitor patients and discontinue HPC, Cord Blood infusion for severe reactions. Use is contraindicated in patients with known allergy to dimethyl sulfoxide (DMSO), Dextran 40 or human serum albumin. [See Contraindications (4) and Warnings and Precautions (5.1, 5.2)]

Graft-vs-host disease (GVHD): GVHD is expected after administration of HPC, Cord Blood, and may be fatal. Administration of immunosuppressive therapy may decrease the risk of GVHD. [See Warnings and Precautions (5.3)]

Engraftment syndrome: Engraftment syndrome may progress to multiorgan failure and death. Treat engraftment syndrome promptly with corticosteroids. [See Warnings and Precautions (5.4)]

Graft failure: Graft failure may be fatal. Monitor patients for laboratory evidence of hematopoietic recovery. Prior to choosing a specific unit of HPC, Cord Blood, consider testing for HLA antibodies to identify patients who are alloimmunized. [See Warnings and Precautions (5.5)]

1 INDICATIONS AND USAGE

HPC (hematopoietic progenitor cells), Cord Blood is an allogeneic cord blood hematopoietic progenitor cell therapy indicated for use in unrelated donor hematopoietic progenitor stem cell transplantation procedures in conjunction with an appropriate preparative regimen for hematopoietic and immunologic reconstitution in patients with disorders affecting the hematopoietic system that are inherited, acquired, or result from myeloablative treatment.

The risk benefit assessment for an individual patient depends on the patient characteristics, including disease, stage, risk factors, and specific manifestations of the disease, on characteristics of the graft, and on other available treatments or types of hematopoietic progenitor cells.

2 DOSAGE AND ADMINISTRATION

For intravenous use only.

Do not irradiate.

2.1 Dosing

The recommended minimum dose is 2.5 x 10^7 nucleated cells/kg at cryopreservation. Multiple units may be required in order to achieve the appropriate dose.

Matching for at least 4 of 6 HLA-A antigens, HLA-B antigens, and HLA-DRB1 alleles is recommended. The HLA typing and nucleated cell content for each individual unit of HPC, Cord Blood are documented on the container label and/or in accompanying records.

2.2 Preparation for Infusion

HPC, Cord Blood should be prepared by a trained healthcare professional.

- Do not irradiate HPC, Cord Blood.
- See the appended detailed instructions for preparation of HPC, Cord Blood for infusion.
- Once prepared for infusion, HPC, Cord Blood may be stored at 1 to 8°C for up to 4 hours.
- The recommended limit on DMSO administration is 1 gram per kg body weight per day. [See Warnings and Precautions (5.2)]

2.3 Administration

HPC, Cord Blood should be administered under the supervision of a qualified healthcare professional experienced in hematopoietic progenitor cell transplantation.

1. Confirm the identity of the patient for the specified unit of HPC, Cord Blood prior to administration.
2. Confirm that emergency medications are available for use in the immediate area.
3. Ensure the patient is hydrated adequately.
4. Premedicate the patient 30 to 60 minutes before the administration of HPC, Cord Blood. Premedications can include any or all of the following: antipyretic, histamine blocker, and corticosteroids.
5. Inspect the product for any abnormalities such as unusual particulates and for breaches of container integrity prior to administration. Prior to infusion, discuss all such product irregularities with the laboratory issuing the product for infusion.
6. Administer HPC, Cord Blood by intravenous infusion. Do not administer in the same tubing concurrently with products other than 0.9% Sodium Chloride, Injection (USP). HPC, Cord Blood may be filtered through a 170 to 260 micron filter designed to remove clots. Do NOT use a filter designed to remove leukocytes.
7. For adults, begin infusion of HPC, Cord Blood at 100 milliliters per hour and increase the rate as tolerated. For children, begin infusion of HPC, Cord Blood at 1 milliliter per kg per hour and increase as tolerated. The infusion rate should be reduced if the fluid load is not tolerated. The infusion should be discontinued in the event of an allergic reaction or if the patient develops a moderate to severe infusion reaction. [See Warnings and Precautions (5) and Adverse Reactions (6)]
8. Monitor the patient for adverse reactions during, and for at least six hours after, administration. Because HPC, Cord Blood contains lysed red cells that may cause renal failure, careful monitoring of urine output is also recommended.

3 DOSAGE FORMS AND STRENGTHS

Each unit of HPC, Cord Blood contains a minimum of 5.0 x 10^8 total nucleated cells with a minimum of 1.25 x 10^6 viable CD34+ cells, suspended in 10% dimethyl sulfoxide (DMSO) and 1% Dextran 40, at the time of cryopreservation.

The exact pre-cryopreservation nucleated cell content is provided on the container label and in accompanying records.

4 CONTRAINDICATIONS

HPC, Cord Blood is contraindicated in patients with known hypersensitivity to dimethyl sulfoxide (DMSO), Dextran 40 or plasma proteins. [See Description (11) and Dosage and Administration (2.2)]

5 WARNINGS AND PRECAUTIONS

5.1 Allergic Reactions and Anaphylaxis

Allergic reactions may occur with infusion of HPC, Cord Blood. Reactions include bronchospasm, wheezing, angioedema, pruritus and hives [see Adverse Reactions (6)]. Serious hypersensitivity reactions, including anaphylaxis, also have been reported. These reactions may be due to dimethyl sulfoxide (DMSO), Dextran 40, or a plasma component of HPC, Cord Blood.

5.2 Infusion Reactions

Infusion reactions are expected to occur and include nausea, vomiting, fever, rigors or chills, flushing, dyspnea, hypoxemia, chest tightness, hypertension, tachycardia, bradycardia, dysgeusia, hematuria, and mild headache. Premedication with antipyretic, histamine antagonists, and corticosteroids may reduce the incidence and intensity of infusion reactions.

Severe reactions, including respiratory distress, severe bronchospasm, severe bradycardia with heart block or other arrhythmias, cardiac arrest, hypotension, hemolysis, elevated liver enzymes, renal compromise, encephalopathy, loss of consciousness, and seizure also may occur. Many of these reactions are related to the amount of DMSO administered. Minimizing the amount of DMSO administered may reduce the risk of such reactions, although idiosyncratic responses may occur even at DMSO doses thought to be tolerated. The actual amount of DMSO depends on the method of preparation of the product for infusion. Limiting the amount of DMSO infused to no more than 1 gm/kg/day is recommended. [See Overdosage (10)]

If infusing more than one unit of HPC, Cord Blood on the same day, do not administer subsequent units until all signs and symptoms of infusion reactions from the prior unit have resolved.

Infusion reactions may begin within minutes of the start of infusion of HPC, Cord Blood, although symptoms may continue to intensify and not peak for several hours after completion of the infusion. Monitor the patient closely during this period. When a reaction occurs, discontinue the infusion and institute supportive care as needed.

5.3 Graft-versus-Host Disease

Acute and chronic graft-versus-host disease (GVHD) may occur in patients who have received HPC, Cord Blood. Classic acute GVHD is manifested as fever, rash, elevated bilirubin and liver enzymes, and diarrhea. Patients transplanted with HPC, Cord Blood also should receive immunosuppressive drugs to decrease the risk of GVHD. [See Adverse Reactions (6.1)

5.4 Engraftment Syndrome

Engraftment syndrome is manifested as unexplained fever and rash in the peri-engraftment period. Patients with engraftment syndrome also may have unexplained weight gain, hypoxemia, and pulmonary infiltrates in the absence of fluid overload or cardiac disease. If untreated, engraftment syndrome may progress to multiorgan failure and death. Begin treatment with corticosteroids once engraftment syndrome is recognized in order to ameliorate the symptoms. [See Adverse Reactions (6.1)]

5.5 Graft Failure

Primary graft failure, which may be fatal, is defined as failure to achieve an absolute neutrophil count greater than 500/uL blood by Day 42 after transplantation. Immunologic rejection is the primary cause of graft failure. Patients should be monitored for laboratory evidence of hematopoietic recovery. Consider testing for HLA antibodies in order to identify patients who are alloimmunized prior to transplantation and to assist with choosing a unit with a suitable HLA type for the individual patient. [See Adverse Reactions (6.1)]

5.6 Malignancies of Donor Origin

Patients who have undergone HPC, Cord Blood transplantation may develop post-transplant lymphoproliferative disorder (PTLD), manifested as a lymphoma-like disease favoring non-nodal sites. PTLD is usually fatal if not treated.

The incidence of PTLD appears to be higher in patients who have received antithymocyte globulin. The etiology is thought to be donor lymphoid cells transformed by Epstein-Barr virus (EBV). Serial monitoring of blood for EBV DNA may be warranted in high-risk groups.

Leukemia of donor origin also has been reported in HPC, Cord Blood recipients. The natural history is presumed to be the same as that for de novo leukemia.

5.7 Transmission of Serious Infections

Transmission of infectious disease may occur because HPC, Cord Blood is derived from human blood. Disease may be caused by known or unknown infectious agents. Donors are screened for increased risk of infection with human immunodeficiency virus (HIV), human T-cell lymphotropic virus (HTLV), hepatitis B virus (HBV), hepatitis C virus (HCV), T. pallidum, T. cruzi, West Nile Virus (WNV), transmissible spongiform encephalopathy (TSE) agents, and vaccinia. Donors are also screened for clinical evidence of sepsis, and communicable disease risks associated with xenotransplantation. Maternal blood samples are tested for HIV types 1 and 2, HTLV types I and II, HBV, HCV, T. pallidum, WNV, and T. cruzi. These measures do not totally eliminate the risk of transmitting these or other transmissible infectious diseases and disease agents. Report the occurrence of a transmitted infection to ClinImmune Labs, University of Colorado Cord Blood Bank (UCCBB) at 303-724-1306.

Testing is also performed for evidence of donor infection due to cytomegalovirus (CMV); however, this is not a donor selection criterion. The result may be found on the container label and/or in accompanying records.

5.8 Transmission of Rare Genetic Diseases

HPC, Cord Blood may transmit rare genetic diseases involving the hematopoietic system for which donor screening and/or testing has not been performed [see Adverse Reactions (6.1)]. Cord blood donors have been screened by family history to exclude inherited disorders of the blood and marrow. HPC, Cord Blood has been tested to exclude donors with sickle cell anemia, and anemias due to abnormalities in hemoglobins C, D, and E. Because of the age of the donor at the time HPC, Cord Blood collection takes place, the ability to exclude rare genetic diseases is severely limited.

6 ADVERSE REACTIONS

Day-100 mortality from all causes was 25%.

The most common infusion-related adverse reactions (≥5%) are hypertension, vomiting, nausea, bradycardia, and fever. (6.1)

6.1 Clinical Trials Experience

Because clinical trials are conducted under widely varying conditions, adverse reaction rates observed in the clinical trials of a drug cannot be directly compared to rates in the clinical trials of another drug and may not reflect the rates observed in practice.

Infusion Reactions

The data described in Table 1 reflect exposure to 442 infusions of HPC, Cord Blood (from multiple cord blood banks) in patients treated using a total nucleated cell dose ≥2.5 x 10^7/kg on a single-arm trial or expanded access use (The COBLT Study). The population was 60% male, and the median age was 5 years (range 0.05-68 years), and included patients treated for hematologic malignancies, inherited metabolic disorders, primary immunodeficiencies, and bone marrow failure. Preparative regimens and graft-vs-host disease prophylaxis were not standardized. The most common infusion reactions were hypertension, vomiting, nausea, and bradycardia. Hypertension and any grades 3-4 infusion-related reactions occurred more frequently in patients receiving volumes greater than 150 milliliters and in pediatric patients. The rate of serious adverse cardiopulmonary reactions was 0.8%.

Table 1. Incidence of Infusion-Related Adverse Reactions Occurring in ≥1% of Infusions (The COBLT Study)
 | Any grade | Grade 3-4
Any reaction | 65.4% | 27.6%
Hypertension | 48.0% | 21.3%
Vomiting | 14.5% | 0.2%
Nausea | 12.7% | 5.7%
Sinus bradycardia | 10.4% | 0
Fever | 5.2% | 0.2%
Sinus tachycardia | 4.5% | 0.2%
Allergy | 3.4% | 0.2%
Hypotension | 2.5% | 0
Hemogloburia | 2.1% | 0
Hypoxia | 2.0% | 2.0%

Information on infusion reactions was available from voluntary reports for 47 patients who received HPC, Cord Blood from ClinImmune Labs at a total nucleated cell dose ≥2.5 x 10^7/kg. The population included 72% males and 28% females, with median age 12 years (range 0.4 - 67.5 years). Preparative regimens and graft-vs-host disease prophylaxis were not standardized. Seventeen patients (36%) had an infusion reaction. Infusion reactions included hypertension, nausea, vomiting, facial flushing, hypoxia, headache, fever and chills, hematuria, and bradycardia.

Other Adverse Reactions

For other adverse reactions, the raw clinical data from the docket were pooled for 1299 patients (120 adult and 1179 pediatric) transplanted with HPC, Cord Blood (from multiple cord blood banks) with total nucleated cell dose ≥2.5 x 10^7/kg. Sixty-six percent (n=862) underwent transplantation as treatment for hematologic malignancy. The preparative regimens and graft-vs-host disease prophylaxis varied. The median total nucleated cell dose was 6.4 (range, 2.5 - 73.8) x 10^7/kg. For these patients, Day-100 mortality from all causes was 25%. Primary graft failure occurred in 16%; 42% developed grades 2 - 4 acute graft-vs-host disease; and 19% developed grades 3-4 acute graft-vs-host disease.

Data from published literature and from observational registries, institutional databases, and cord blood bank reviews reported to the docket for HPC, Cord Blood (from multiple cord blood banks) revealed nine cases of donor cell leukemia, one case of transmission of infection, and one report of transplantation from a donor with an inheritable genetic disorder. The data are not sufficient to support reliable estimates of the incidences of these events.

In a study of 364 patients, 15% of the patients developed engraftment syndrome.

8 USE IN SPECIFIC POPULATIONS

8.1 Pregnancy

Pregnancy Category C. Animal reproduction studies have not been conducted with HPC, Cord Blood. It is also not known whether HPC, Cord Blood can cause fetal harm when administered to a pregnant woman or can affect reproduction capacity. There are no adequate and well-controlled studies in pregnant women. HPC, Cord Blood should be used during pregnancy only if the potential benefit justifies the potential risk to the fetus.

8.4 Pediatric Use

HPC, Cord Blood has been used in pediatric patients with disorders affecting the hematopoietic system that are inherited, acquired, or resulted from myeloablative treatment. [See Dosage and Administration (2), Adverse Reactions (6), and Clinical Studies (14)]

8.5 Geriatric Use

Clinical studies of HPC, Cord Blood (from multiple cord blood banks) did not include sufficient numbers of subjects aged 65 and over to determine whether they respond differently than younger subjects. In general, administration of HPC, Cord Blood to patients over age 65 should be cautious, reflecting their greater frequency of decreased hepatic, renal, or cardiac function, and of concomitant disease or other drug therapy.

8.6 Renal Disease

HPC, Cord Blood contains Dextran 40 which is eliminated by the kidneys. The safety of HPC, Cord Blood has not been established in patients with renal insufficiency or renal failure.

10 OVERDOSAGE

10.1 Human Overdosage Experience

There has been no experience with overdosage of HPC, Cord Blood in human clinical trials. Single doses of HPC, Cord Blood from ClinImmune Labs up to 6.5 x 10^8 TNC/kg have been administered. HPC, Cord Blood prepared for infusion may contain dimethyl sulfoxide (DMSO). The maximum tolerated dose of DMSO has not been established, but it is customary not to exceed a DMSO dose of 1 gm/kg/day when given intravenously. Several cases of altered mental status and coma have been reported with higher doses of DMSO.

10.2 Management of Overdose

For DMSO overdosage, general supportive care is indicated. The role of other interventions to treat DMSO overdosage has not been established.

11 DESCRIPTION

HPC, Cord Blood consists of hematopoietic progenitor cells, monocytes, lymphocytes, and granulocytes from human cord blood. Blood recovered from umbilical cord and placenta is volume reduced and partially depleted of red blood cells and plasma.

The active ingredient is hematopoietic progenitor cells which express the cell surface marker CD34. The potency of cord blood is determined by measuring the numbers of total nucleated cells (TNC) and CD34+ cells, and cell viability. Each unit of HPC, Cord Blood contains a minimum of 5 x 10^8 total nucleated cells with at least 1.25 x 10^6 viable CD34+ cells at the time of cryopreservation. The cellular composition of HPC, Cord Blood depends on the composition of cells in the blood recovered from the umbilical cord and placenta of the donor. The actual nucleated cell count, the CD34^+ cell count, the ABO group, and the HLA typing are listed on the container label and/or accompanying records sent with each individual unit.

HPC, Cord Blood has the following inactive ingredients: dimethyl sulfoxide (DMSO) and Dextran 40. When prepared for infusion according to instructions, the infusate contains the following inactive ingredients: Dextran 40, human serum albumin, and residual DMSO.

12 CLINICAL PHARMACOLOGY

12.1 Mechanism of Action

Hematopoietic stem/progenitor cells from HPC, Cord Blood migrate to the bone marrow where they divide and mature. The mature cells are released into the bloodstream, where some circulate and others migrate to tissue sites, partially or fully restoring blood counts and function, including immune function, of blood-borne cells of marrow origin. [See Clinical Studies (14)]

In patients with enzymatic abnormalities due to certain severe types of storage disorders, mature leukocytes resulting from HPC, Cord Blood transplantation may synthesize enzymes that may be able to circulate and improve cellular functions of some native tissues. However, the precise mechanism of action is unknown.

14 CLINICAL STUDIES

The effectiveness of HPC, Cord Blood, as defined by hematopoietic reconstitution, was demonstrated in one single-arm prospective study and in retrospective reviews of data from an observational database for HPC, Cord Blood and data in the dockets and public information. Sixty-six percent (n=862) of the 1299 patients in the docket and public data underwent transplantation as treatment for hematologic malignancy. Results for patients who received a total nucleated cell dose ≥2.5 x 10^7/kg are shown in Table 2. Neutrophil recovery is defined as the time from transplantation to an absolute neutrophil count more than 500 per microliter. Platelet recovery is the time to a platelet count more than 20,000 per microliter. Erythrocyte recovery is the time to a reticulocyte count greater than 30,000 per microliter. The total nucleated cell dose and degree of HLA mismatch were inversely associated with the time to neutrophil recovery in the docket data.

Table 2. Hematopoietic Recovery for Patients Transplanted with Total Nucleated Cell (TNC) Dose ≥ 2.5 x 10^7/kg
Data Source | The COBLT Study* | Docket* and Public Data* | ClinImmune Labs HPC, Cord Blood
Design | Single-arm prospective | Retrospective | Retrospective
Number of patients | 324 | 1299 | 220
Median age (range) | 4.6 (0.07 – 52.2) yrs | 7.0 (<1 – 65.7) yrs | 6.9 (0.1 – 73.1) yrs
Gender | 59% male 41% female | 57% male 43% female | 57% male 43% female
Median TNC Dose (range) (x 10^7/kg) | 6.7 (2.6 – 38.8) | 6.4 (2.5 – 73.8) | 5.8 (2.5 – 65.0)
Neutrophil Recovery at Day 42 | 76% (95% CI 71% – 81%) | 77% (95% CI 75% – 79%) | 79% (95% CI 73.5%- 84.4%)
Platelet Recovery at Day 100 (20,000/uL) | 57% (95% CI 51% – 63%) | - | 62% (95% CI 44.8%-77.5%)
Platelet Recovery at Day 100 (50,000/uL) | 46% (95% CI 39% – 51%) | 45% (95% CI 42% – 48%) | 55% (95% CI 36.0%-72.7%)
Erythrocyte Recovery at Day 100 | 65% (95% CI 58% – 71%) | - | -
Median time to Neutrophil Recovery | 27 days | 25 days | 25 days
Median time to Platelet Recovery (20,000/uL) | 90 days | - | 55 days
Median time to Platelet Recovery (50,000/uL) | 113 days | 122 days | 49 days
Median time to Erythrocyte Recovery | 64 days | - | -
* HPC, Cord Blood (from multiple cord blood banks)

16 HOW SUPPLIED/STORAGE AND HANDLING

HPC, Cord Blood is supplied as a cryopreserved cell suspension in a sealed bag containing a minimum of 5 x 10^8 total nucleated cells with a minimum of 1.25 x 10^6 viable CD34+ cells in a volume of 30-124 milliliters (ISBT 128 Product Code S1393, ISBT 128 Facility Identifier Number W3213). The exact pre-cryopreservation volume and nucleated cell content are provided on the container label and accompanying records.

Store HPC, Cord Blood at or below -150°C until ready for thawing and preparation.

17 PATIENT COUNSELING INFORMATION

Discuss the following with patients receiving HPC, Cord Blood:

- Report immediately any signs and symptoms of acute infusion reactions, such as fever, chills, fatigue, breathing problems, dizziness, nausea, vomiting, headache, or muscle aches.
- Report immediately any signs or symptoms suggestive of graft-vs-host disease, including rash, diarrhea, or yellowing of the eyes.

INSTRUCTIONS FOR PREPARATION FOR INFUSION

1 Equipment, reagents, Materials, and forms

Equipment
Water bath
Plasma Extractor
Centrifuge - refrigerated
Balance
Tubing stripers
Sealer
Hemocytometer chamber
Cell counter
Thermometer

Reagents
5% Albumin (human), USP
10% Dextran 40 in Sodium Chloride Solution, USP

Materials
Plasma transfer set
150 mL double transfer pack, 150 mL transfer pack, or 300 mL transfer pack
Centrifuge bag
Plastic tubing clip
Sterile disposable syringes: 1, 5, 10, 20, 30, and 60 mL
18 gauge needle
70% isopropyl alcohol
Sterile water

Forms Provided by ClinImmune Labs
Transplant Center Hematopoietic Progenitor Cells, Cord Blood (HPC, Cord Blood) Thaw Worksheet
Form E5.103 - HPC, Cord Blood Release Report
Form E6.251 - Human Cord Blood Unit Receipt Form
Form E8.102 - Adverse Product Event and Infusion Reaction

2 ADMINISTRATIVE REQUIREMENTS

1. Immediately following receipt of product - Complete Form E6.251 – HPC Unit Receipt Form and fax it to ClinImmune Labs (303-724-1849). Document:
  - Patient's name, medical record number
  - Date and time prior to opening the dry shipper
  - Weight of the dry shipper
  - Match of the HPC, Cord Blood identification number expected with the HPC, Cord Blood number received
  - Condition of the HPC, Cord Blood upon arrival (i.e., still frozen)
  - Internal temperature of the dry shipper
  - Transplant facility information
  - Comments and/or explanation for any deviations
2. Prior to thawing - Review and complete all transport verification to document receipt of the unit against Form E5-103 – HPC, Cord Blood Release Report. If there are any errors or ambiguity, do not proceed. Report any problems to ClinImmune Labs (303-724-1306) and the transplant physician.
3. During thawing - Complete the thaw worksheet.
4. Ensure that Form E8.102 (Adverse Product Event and Infusion Reaction) accompanies the product to the transplant unit.
5. Return the dry shipper as soon as possible. After transplant, return the metal canister at earliest convenience.

Contact Information for ClinImmune Labs at the University of Colorado Cord Blood Bank (UCCBB):

UCCBB

1999 North Fitzsimmons Parkway, Suite 160

Aurora, CO 80045

Cord Blood Bank Hours: Monday – Friday, 8:00 AM – 5:00 PM (Mountain Time)

Cord Blood Bank Phone Number: 303-724-1306

Cord Blood Bank Fax Number: 303-724-1849

Pagers:

Cord Blood Bank Coordinator

303-266-0254

Cord Blood Bank Director

303-266-3043

Cord Blood Bank Medical Director

303-266-0763 or 303-540-1914

3 VERIFICATION OF PRODUCT IDENTITY

HPC, Cord Blood is shipped frozen in an overwrap in the metal canister. HPC, Cord Blood must be kept at or below -150° C, either inside the container used for shipping (Dry-Shipper) or in vapor phase of a Liquid Nitrogen (LN2) storage device at the Transplant Center (recommended).

1. Check the HPC, Cord Blood identification number (ID) on the label to confirm its identity with the ID of the expected product as soon as it is received (Figure 1).
  Figure 1
2. Wearing protective cryogloves, transfer the HPC, Cord Blood from the Dry-Shipper to the vapor phase of a LN2 storage tank.
3. Carefully open the canister while it is in the vapor of the freezer to prevent the bag from cracking and the yellow port covers from popping off (Figure 2).
  Figure 2
4. Work carefully to avoid damaging the frozen plastic product bag.
5. Check the bar-coded label on the product against your records to verify that the bar code and visually-readable printed number absolutely conforms to the information previously provided and the documentation included with the HPC, Cord Blood product (Form E6.251 - Human Cord Blood Unit Receipt Form).

NOTE: | If there is any error or ambiguity with regard to the product ID, close the canister and keep the product at LN2 temperature. Immediately advise the staff of ClinImmune Labs, UCCBB and the transplant physician. Do not proceed until the problem is resolved. If your LN2 storage tanks have no space to store the product in its canister, add LN2 to the UCCBB dry-shipper to maintain the product frozen until a completely satisfactory determination is made.

4 METHOD

4.1 Preparation of Water Bath

1. A water bath with minimum 2 L capacity is recommended.
2. Clean water bath with 70% isopropyl alcohol and fill with appropriate volume of sterile water.
3. Maintain the temperature of the water bath between 36-38°C prior to thawing the HPC, Cord Blood.

4.2 Preparation of Wash Media

1. Prepare wash media no sooner than one hour prior to the thaw for infusion. Media expires 4 hours after preparation.
2. Determine the total volume of media needed. For reconstitution only, use an equal volume of media to the total HPC, Cord Blood cryo volume. For wash and reconstitution, use twice the total HPC, Cord Blood cryo volume.
  Example: 50 mL of HPC, Cord Blood cryo volume
  For reconstitution only: 50 mL of media are needed.
  For reconstitution and wash: 100 mL of media are needed.
3. Prepare the media by mixing equal amounts of 5% albumin and 10% Dextran 40.
  Example: To prepare 50 mL of media, mix 25 mL of 5% albumin and 25 mL of 10% Dextran 40.

4.3 Thawing HPC, Cord Blood

1. Carefully cut and remove the overwrap (Figures 3, 4, and 5).
  Figure 3
  Figure 4
  Figure 5
2. Put the HPC, Cord Blood into a sterile centrifuge bag and place HPC, Cord Blood in the water bath. If there are two cryo bags for the same HPC, Cord Blood, thaw both bags in separate sterile centrifuge bags at the same time.
3. Thaw the HPC, Cord Blood until all frozen portions dissolve into solution.
4. Take the bag(s) out of the water bath, remove the HPC, Cord Blood from the sterile bag(s), and place it into a laminar flow hood.
5. To access a bag with a configuration as shown in Figures 6 and 7, remove the yellow port protector and insert a plasma transfer set into the port. For a bag with configuration as shown in Figure 8, open the port by twisting the upper part of the port.
6. Measure the volume by syringe or weight as per transplant center procedures.
7. Remove a small volume for quality control (QC) testing as per transplant center procedures. If the HPC, Cord Blood has two cryo bags, pool both portions together in the same transfer bag before removing the sample.
  Figure 6
  Figure 7
  Figure 8
8. The thawed HPC, Cord Blood is ready for reconstitution or washing (see below).

4.4 Reconstituting and Washing HPC, Cord Blood

For reconstituting HPC, Cord Blood (dilution)

1. If using a 150 mL double transfer pack, clamp off one of the bags with a plastic clip and drain the HPC, Cord Blood into the open transfer bag (Figure 9).
  Figure 9
  For two cryo bags, drain both bags into the double transfer bag or use a 300 mL transfer bag.
2. Use a hemostat to clamp the line to the transfer bag containing the HPC, Cord Blood.
3. Wash the cryo bag by injecting the wash media (equal to the total volume of the frozen HPC, Cord Blood) into the empty bag and rinsing thoroughly (Figure 10).
  Figure 10
4. Open the hemostat and slowly drain the wash media into the bag with the HPC, Cord Blood while gently mixing the cells in the bag with a rocking motion. Seal off the empty freezing bag.
5. Remove a small volume of the reconstituted product for QC testing (such as complete blood count (CBC), CFU, CD34+ counts, viability, and sterility) as per transplant center procedures.
6. Allow five minutes for the cells to equilibrate.
7. HPC, Cord Blood is ready for infusion or for washing out the cryoprotectant.
8. The recommended expiration time is four hours at 1-8°C from the time of thaw.

For removing cryoprotectant (washing)

1. Centrifuge the diluted HPC, Cord Blood (with ports up) at 1300 rpm (473 x g) for ten minutes at 1-6°C.
2. Remove the supernatant (equal volume of added wash media) using a plasma extractor (Figure 11).
  Figure 11
3. Slowly add the remaining washing media (that was not used in reconstitution).
4. Mix the bag gently.
5. Remove a small volume of the reconstituted product for QC testing (such as CBC, CFU, CD34+ counts, viability, and sterility) as per transplant center procedures.
6. HPC, Cord Blood is ready for infusion.
7. The recommended expiration time is four hours at 1-8°C from the time of thaw.

5. EMERGENCY PRODUCT RECOVERY IN THE EVENT OF A CONTAINER FAILURE

1. Emergency product recovery at transport: If the alarm is blinking red upon receipt of the dry shipper, document on Form E6.251 and immediately use an alternative means to monitor and document the dry shipper temperature. If the temperature is higher than -150°C and there are ice crystals observed in the HPC, Cord Blood, immediately store the HPC, Cord Blood in liquid nitrogen vapor phase and notify the transplant physician. Document the temperature on Form E6.251 and notify ClinImmune Labs, University of Colorado Cord Blood Bank immediately at 303-724-1306.
2. Emergency product recovery at thaw: If any cracks or port integrity leaks are observed in the cryo bag at thaw, remove the HPC, Cord Blood from the water bath and clamp off the leaking portion of the bag with a hemostat. If the HPC, Cord Blood is still frozen, continue to thaw the product with the leaking site clamped tightly. Once thawed, remove the HPC, Cord Blood from the water bath, recover cells in the sterile thawing bag if there are any, and contact the appropriate transplant center staff immediately for further instruction. Document all findings on Form E8.102 and fax it to the ClinImmune Labs, University of Colorado Cord Blood Bank at 303-724-1849

Distributed by:
ClinImmune Labs
University of Colorado Cord Blood Bank (UCCBB)
1999 North Fitzsimmons Parkway, Suite 160
Aurora, CO 80045
US License #1855

Issued: 05/2012

Principal Display Panel – Bag Label

HPC, Cord Blood
Approx & VOL.: mL
Additives & Vol.: mL DMSO
DEXTRAN. < mL HESPAN
< mL CPD. EtO may persist
For Intravenous Infusion
Do Not Irradiate
Do Not Use Leukoreduction Filters
Store at <= -150C

Caution: Federal Law prohibits
distribution without a prescription

ClinImmune Labs – UCCBB
12635 E. Montview Blvd.
Aurora, CO 80045